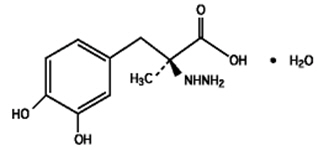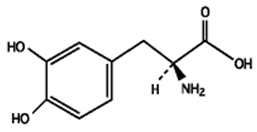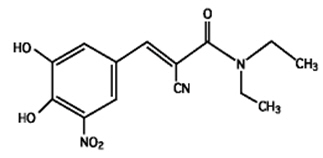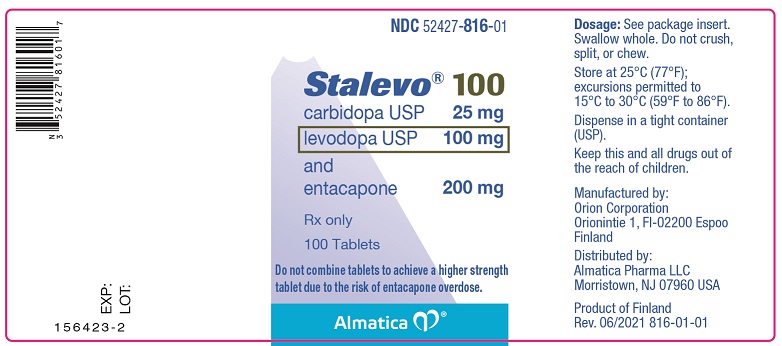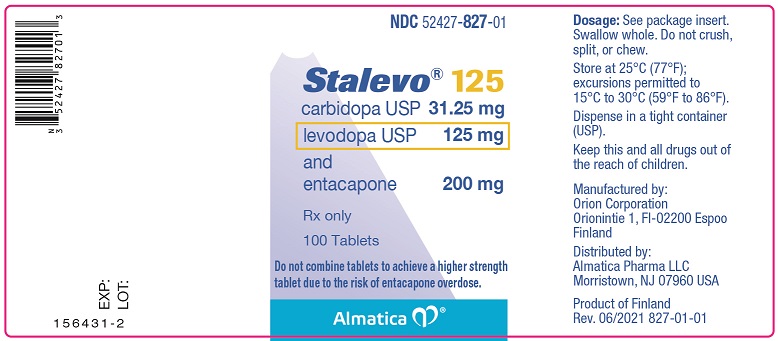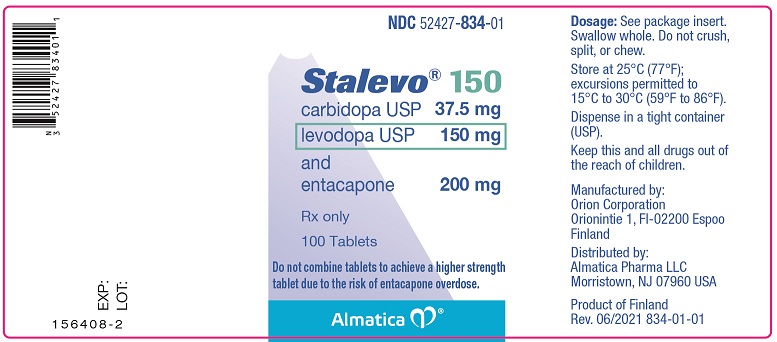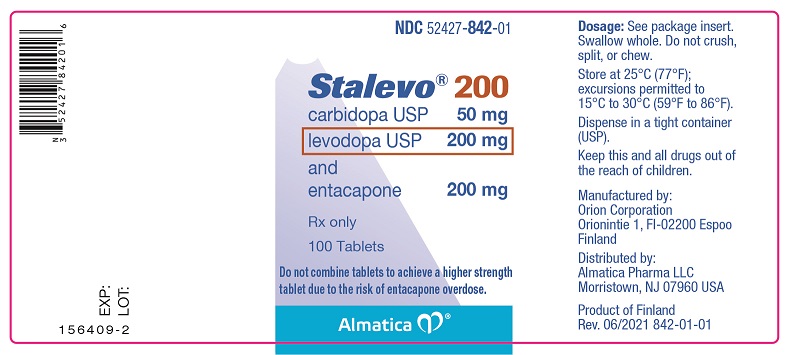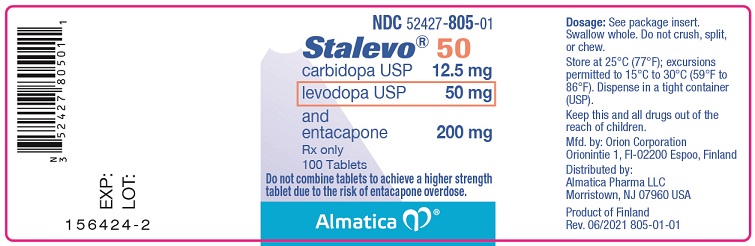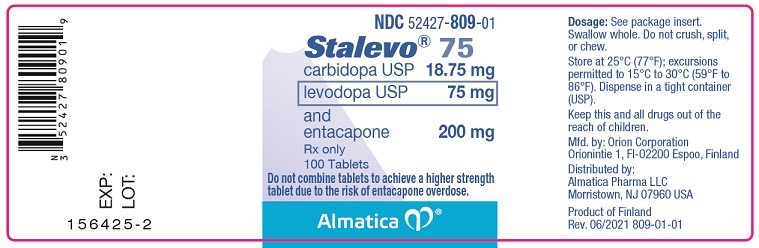 DRUG LABEL: Stalevo
NDC: 52427-805 | Form: TABLET, FILM COATED
Manufacturer: Almatica Pharma LLC
Category: prescription | Type: HUMAN PRESCRIPTION DRUG LABEL
Date: 20210730

ACTIVE INGREDIENTS: carbidopa 12.5 mg/1 1; levodopa 50 mg/1 1; entacapone 200 mg/1 1
INACTIVE INGREDIENTS: starch, corn; croscarmellose sodium; glycerin; hypromellose, unspecified; magnesium stearate; mannitol; polysorbate 80; povidone, unspecified; sucrose; ferric oxide red; titanium dioxide; ferric oxide yellow

HIGHLIGHTS OF PRESCRIBING INFORMATION

These highlights do not include all the information needed to use STALEVO safely and effectively. See full prescribing information for STALEVO.
STALEVO® (carbidopa, levodopa and entacapone) tablets, for oral use
Initial U.S. Approval: 2003

1 INDICATIONS AND USAGE

Stalevo, a combination drug consisting of levodopa (aromatic amino acid), carbidopa (aromatic amino acid decarboxylation inhibitor), and entacapone (catechol-O-methyltransferase (COMT) inhibitor) is indicated for the treatment of Parkinson's disease. Stalevo is to be used:

- To substitute (with equivalent strengths of each of the three components) for carbidopa/levodopa and entacapone previously administered as individual products (1)
- To replace carbidopa/levodopa therapy (without entacapone) when patients experience the signs and symptoms of end-of-dose "wearing-off" and when they have been taking a total daily dose of levodopa of 600 mg or less and have not been experiencing dyskinesias (1)

2 DOSAGE AND ADMINISTRATION

- The optimum daily dosage of Stalevo must be determined by careful titration in each patient (2.1)
- Individual tablets should not be split or fractionated. Administer only one tablet at each dosing interval (2.6)

3 DOSAGE FORMS AND STRENGTHS

Each Stalevo tablet contains a 1:4 ratio of carbidopa to levodopa and 200 mg of entacapone (mg of carbidopa per mg of levodopa per mg of entacapone)

- Stalevo 50 (12.5 mg per 50 mg per 200 mg)
- Stalevo 75 (18.75 mg per 75 mg per 200 mg)
- Stalevo 100 (25 mg per 100 mg per 200 mg)
- Stalevo 125 (31.25 mg per 125 mg per 200 mg)
- Stalevo 150 (37.5 mg per 150 mg per 200 mg)
- Stalevo 200 (50 mg per 200 mg per 200 mg)

4 CONTRAINDICATIONS

- Concomitant use of nonselective monoamine oxidase (MAO) inhibitors (4)
- Narrow-angle glaucoma (4)

5 WARNINGS AND PRECAUTIONS

- May cause falling asleep during activities of daily living without apparent warning, and daytime drowsiness and somnolence (5.1)
- May cause syncope and hypotension/orthostatic hypotension (5.2)
- May cause or exacerbate dyskinesia (5.3)
- May cause depression and suicidality (5.4)
- May cause hallucinations and/or other psychotic-like behavior (5.5)
- May cause problems with impulse control and compulsive behaviors (5.6)
- Abrupt discontinuation may cause hyperpyrexia and confusion (5.7)
- May cause diarrhea and/or drug-induced colitis (5.8)
- May cause rhabdomyolysis (5.9)

6 ADVERSE REACTIONS

The most common adverse reactions (incidence 3% higher than placebo incidence) are dyskinesias, hyperkinesia, diarrhea, nausea, abdominal pain, vomiting, dry mouth and urine discoloration (6.1)

To report SUSPECTED ADVERSE REACTIONS, contact Almatica Pharma LLC at 1-877-447-7979 or FDA at 1-800-FDA-1088 or www.fda.gov/medwatch.

7 DRUG INTERACTIONS

- Drugs metabolized by COMT: use with caution (5.11,7.2)
- Anti-hypertensive agents: dose adjustment may be required (7.3)
- Tricyclic antidepressants: risk of hypertension and dyskinesia reported during concomitant use with carbidopa/levodopa (7.4)
- Dopamine D2 receptor antagonists, isoniazid, phenytoin, papaverine and iron salts: may reduce efficacy of Stalevo (7.5, 7.6, 7.7, 7.8, 7.9)
- Drugs that interfere with biliary excretion, glucuronidation and intestinal beta-glucuronidase: dose adjustment of Stalevo may be required (7.10)
- Drugs metabolized by CYP2C9 (e.g., coumadin): dose adjustment of Stalevo may be required; monitor INR when initiating Stalevo in patients on coumadin (7.11)

8 USE IN SPECIFIC POPULATIONS

- Pregnancy: based on animal data, may cause fetal harm (8.1)

FULL PRESCRIBING INFORMATION

1 INDICATIONS AND USAGE

Stalevo is indicated for the treatment of Parkinson's disease.

Stalevo can be used:

- To substitute (with equivalent strengths of each of the three components) carbidopa/levodopa and entacapone previously administered as individual products.
- To replace carbidopa/levodopa therapy (without entacapone) when patients experience the signs and symptoms of end-of-dose "wearing-off" and when they have been taking a total daily dose of levodopa of 600 mg or less and have not been experiencing dyskinesias.

2 DOSAGE AND ADMINISTRATION

Stalevo should be used as a substitute for patients already stabilized on equivalent doses of carbidopa/levodopa and entacapone. However, some patients who have been stabilized on a given dose of carbidopa/levodopa may be treated with Stalevo if a decision has been made to add entacapone (see below). Therapy should be individualized and adjusted according to the desired therapeutic response.

2.1 Dosing Information

The optimum daily dosage of Stalevo must be determined by careful titration in each patient.

Clinical experience with daily doses above 1,600 mg of entacapone is limited. The maximum recommended daily dose of Stalevo depends on the strength used. The maximum number of tablets to be used in a 24-hour period is less with the highest strength (Stalevo 200) than with lower strengths (see Table 1). Studies show that peripheral dopa decarboxylase is saturated by carbidopa at approximately 70 mg per day to 100 mg per day. Patients receiving less than this amount of carbidopa are more likely to experience nausea and vomiting.

Table 1: Maximum Recommended Dose of Stalevo in a 24-hour Period
Stalevo Dosage Strength | Maximum Number of Tablets in a 24-hour Period
Stalevo 50, Stalevo 75, Stalevo 100, Stalevo 125, Stalevo 150 | 8
Stalevo 200 | 6

2.2 Converting Patients from Carbidopa, Levodopa, and Entacapone to Stalevo

Patients currently treated with entacapone 200 mg with each dose of non-extended release carbidopa/levodopa tablet, can switch to the corresponding strength of Stalevo containing the same amounts of levodopa and carbidopa. For example, patients receiving one tablet of carbidopa/levodopa 25 mg/100 mg and one tablet of entacapone 200 mg at each administration can switch to a single Stalevo 100 tablet (containing 25 mg of carbidopa, 100 mg of levodopa and 200 mg of entacapone).

2.3 Converting Patients from Carbidopa and Levodopa Products to Stalevo

There is no experience in transferring patients currently treated with extended release formulations of carbidopa/levodopa, or carbidopa/levodopa products that are not combined in a 1:4 ratio of carbidopa to levodopa.

Patients with a history of moderate or severe dyskinesias or taking more than 600 mg of the levodopa component per day are likely to require a reduction in their daily levodopa dose when entacapone is added. Because dose adjustment of the individual carbidopa or levodopa component is not possible with fixed-dose products, initially titrate patients to a dose that is tolerated and that meets their individual therapeutic need using a separate carbidopa/levodopa tablet (1:4 ratio) plus an entacapone tablet. Once the patient's individual dose of carbidopa/levodopa plus entacapone dose has been established using two separate tablets; switch the patient to a corresponding single tablet of Stalevo.

When less levodopa is required, reduce the total daily dosage of carbidopa/levodopa either by decreasing the strength of Stalevo at each administration or by decreasing the frequency of administration by extending the time between doses.

2.4 Concomitant Use with Other Anti-Parkinson's Disease Drugs

Anticholinergic agents, dopamine agonists, monoamine oxidase (MAO) - B inhibitors, amantadine, and other standard drugs for Parkinson's disease may be used concomitantly while Stalevo is being administered; however, dosage adjustments of the concomitant medication or Stalevo may be required.

2.5 Decrease or Interruption of Dosing

Avoid interruption of Stalevo dosing because hyperpyrexia has been reported in patients who suddenly discontinue or reduce their use of levodopa [see Warnings and Precautions (5.7)].

2.6 Important Administration Instructions

Do not split, crush or chew Stalevo tablets. Administer only one tablet at each dosing interval. All strengths of Stalevo contain 200 mg of entacapone. Combining multiple tablets or portions of tablets to achieve a higher levodopa dose may lead to an overdose of entacapone.

Administer Stalevo with or without food. However, a high-fat, high-calorie meal may delay the absorption of levodopa by about 2 hours [see Clinical Pharmacology (12.3)].

3 DOSAGE FORMS AND STRENGTHS

Each Stalevo tablet, provided in 6 single-dose strengths, contains carbidopa and levodopa in a 1:4 ratio and a 200 mg dose of entacapone. Stalevo (carbidopa, levodopa and entacapone) is supplied as film-coated tablets for oral administration in the following 6 strengths:

Stalevo 50 film-coated tablets containing 12.5 mg of carbidopa, 50 mg of levodopa and 200 mg of entacapone. The round, bi-convex shaped tablets are brownish- or greyish-red, unscored, and embossed "LCE 50" on one side.

Stalevo 75 film-coated tablets containing 18.75 mg of carbidopa, 75 mg of levodopa and 200 mg of entacapone. The oval-shaped tablets are light brownish red, unscored and embossed with code "LCE 75" on one side.

Stalevo 100 film-coated tablets containing 25 mg of carbidopa, 100 mg of levodopa and 200 mg of entacapone. The oval-shaped tablets are brownish- or greyish-red, unscored, and embossed "LCE 100" on one side.

Stalevo 125 film-coated tablets containing 31.25 mg of carbidopa, 125 mg of levodopa and 200 mg of entacapone. The oval-shaped tablets are light brownish red, unscored and embossed with code "LCE 125" on one side.

Stalevo 150 film-coated tablets containing 37.5 mg of carbidopa, 150 mg of levodopa and 200 mg of entacapone. The elongated-ellipse shaped tablets are brownish- or greyish-red, unscored, and embossed "LCE 150" on one side.

Stalevo 200 film-coated tablets containing 50 mg of carbidopa, 200 mg of levodopa and 200 mg of entacapone. The oval shaped tablets are dark brownish red, unscored, and embossed "LCE 200" on one side.

4 CONTRAINDICATIONS

Stalevo is contraindicated in patients:

- Taking nonselective monoamine oxidase (MAO) inhibitors (e.g., phenelzine and tranylcypromine). These nonselective MAO inhibitors must be discontinued at least two weeks prior to initiating therapy with Stalevo.
- With narrow-angle glaucoma.

5 WARNINGS AND PRECAUTIONS

The following adverse reactions described in this section are related to at least one of the components of Stalevo (i.e., levodopa, carbidopa, and/or entacapone) based upon the safety experience in clinical trials (especially pivotal trials) or in postmarketing reports.

5.1 Falling Asleep During Activities of Daily Living and Somnolence

Patients with Parkinson's disease treated with Stalevo or other carbidopa/levodopa products have reported suddenly falling asleep without prior warning of sleepiness while engaged in activities of daily living (including the operation of motor vehicles). Some of these episodes resulted in accidents. Although many of these patients reported somnolence while taking entacapone, some did not perceive warning signs, such as excessive drowsiness, and believed that they were alert immediately prior to the event. Some of these events have been reported to occur up to one year after initiation of treatment.

Somnolence was reported in 2% of patients taking entacapone and 0% in placebo in controlled trials. It is reported that falling asleep while engaged in activities of daily living always occurs in a setting of pre-existing somnolence, although patients may not give such a history. For this reason, prescribers should reassess patients for drowsiness or sleepiness especially since some of the events occur well after the start of treatment. Prescribers should also be aware that patients may not acknowledge drowsiness or sleepiness until directly questioned about drowsiness or sleepiness during specific activities. Patients who have already experienced somnolence and/or an episode of sudden sleep onset should not participate in these activities during treatment with Stalevo.

Before initiating treatment with Stalevo, advise patients of the potential to develop drowsiness and specifically ask about factors that may increase this risk such as use of concomitant sedating medications and the presence of sleep disorders. If a patient develops daytime sleepiness or episodes of falling asleep during activities that require active participation (e.g., conversations, eating, etc.), Stalevo should ordinarily be discontinued [see Dosage and Administration (2.5) and Warnings and Precautions (5.7)]. If the decision is made to continue Stalevo, patients should be advised not to drive and to avoid other potentially dangerous activities. There is insufficient information to establish whether dose reduction will eliminate episodes of falling asleep while engaged in activities of daily living.

5.2 Hypotension, Orthostatic Hypotension and Syncope

Reports of syncope were generally more frequent in patients in both treatment groups who had had a prior episode of documented hypotension (although the episodes of syncope, obtained by history, were themselves not documented with vital sign measurement). Hypotension, orthostatic hypotension, and syncope are observed in patients treated with drugs that increase central dopaminergic tone including Stalevo.

5.3 Dyskinesia

Dyskinesia (involuntary movements) may occur or be exacerbated at lower dosages and sooner with Stalevo than with preparations containing only carbidopa and levodopa. The occurrence of dyskinesias may require dosage reduction.

In pivotal trials, the treatment difference incidence of dyskinesia was 10% and for carbidopa-levodopa plus 200 mg entacapone. Although decreasing the dose of levodopa may ameliorate this side effect, many patients in controlled trials continued to experience frequent dyskinesias despite a reduction in their dose of levodopa. The treatment difference incidence of study withdrawal for dyskinesia was 1% for carbidopa-levodopa-entacapone.

5.4 Depression and Suicidality

All patients should be observed carefully for the development of depression with concomitant suicidal tendencies. Patients with past or current psychoses should be treated with caution.

5.5 Hallucinations and/or Psychotic-Like Behavior

Dopaminergic therapy in patients with Parkinson's disease has been associated with hallucinations. Hallucinations led to drug discontinuation and premature withdrawal from clinical trials in 0.8% and 0% of patients treated with carbidopa, levodopa, entacapone and carbidopa, levodopa, respectively. Hallucinations led to hospitalization in 1.0% and 0.3% of patients in the carbidopa, levodopa, entacapone and carbidopa, levodopa, groups, respectively. Agitation occurred in 1% of patients treated with carbidopa, levodopa, entacapone and 0% treated with carbidopa, levodopa.

5.6 Impulse Control and/or Compulsive Behaviors

Postmarketing reports suggest that patients treated with anti-Parkinson medications can experience intense urges to gamble, increased sexual urges, intense urges to spend money uncontrollably, and other intense urges. Patients may be unable to control these urges while taking one or more of the medications generally used for the treatment of Parkinson's disease and which increase central dopaminergic tone, including entacapone taken with levodopa and carbidopa. In some cases, although not all, these urges were reported to have stopped when the dose of anti-Parkinson medications was reduced or discontinued. Because patients may not recognize these behaviors as abnormal it is important for prescribers to specifically ask patients or their caregivers about the development of new or increased gambling urges, sexual urges, uncontrolled spending or other urges while being treated with entacapone. Physicians should consider dose reduction or stopping Stalevo if a patient develops such urges while taking Stalevo [see Dosage and Administration (2.5), Warnings and Precautions (5.7)].

5.7 Withdrawal-Emergent Hyperpyrexia and Confusion

Cases of hyperpyrexia and confusion resembling neuroleptic malignant syndrome (NMS) have been reported in association with dose reduction or withdrawal of therapy with carbidopa, levodopa and entacapone. However, in some cases, hyperpyrexia and confusion were reported after initiation of treatment with entacapone. Hyperpyrexia and confusion are uncommon but they may be life-threatening with a variety of features, including hyperpyrexia/fever/hyperthermia, muscle rigidity, involuntary movements, altered consciousness/mental status changes, delirium, autonomic dysfunction, tachycardia, tachypnea, sweating, hyper- or hypotension, and abnormal laboratory findings (e.g., creatine phosphokinase elevation, leukocytosis, myoglobinuria, and increased serum myoglobin).

If a patient needs to discontinue or reduce their daily dose of Stalevo, the dose should be decreased slowly, with supervision from a health care provider [see Dosage and Administration (2.5)]. Specific methods for tapering entacapone have not been systematically evaluated.

5.8 Diarrhea and Colitis

In clinical trials of entacapone, diarrhea developed in 60 of 603 (10.0%) and 16 of 400 (4.0%) of patients treated with 200 mg of entacapone or placebo in combination with levodopa and dopa decarboxylase inhibitor, respectively. In patients treated with entacapone, diarrhea was generally mild to moderate in severity (8.6%) but was regarded as severe in 1.3%. Diarrhea resulted in withdrawal in 10 of 603 (1.7%) patients, 7 (1.2%) with mild and moderate diarrhea and 3 (0.5%) with severe diarrhea. Diarrhea generally resolved after discontinuation of entacapone. Two patients with diarrhea were hospitalized. Typically, diarrhea presents within 4 to 12 weeks after entacapone is started, but it may appear as early as the first week and as late as many months after the initiation of treatment. Diarrhea may be associated with weight loss, dehydration, and hypokalemia.

Postmarketing experience has shown that diarrhea may be a sign of drug-induced microscopic colitis, primarily lymphocytic colitis. In these cases diarrhea has usually been moderate to severe, watery and non-bloody, at times associated with dehydration, abdominal pain, weight loss, and hypokalemia. In the majority of cases, diarrhea and other colitis-related symptoms resolved or significantly improved when entacapone treatment was stopped. In some patients with biopsy confirmed colitis, diarrhea had resolved or significantly improved after discontinuation of entacapone but recurred after retreatment with entacapone.

If prolonged diarrhea is suspected to be related to Stalevo, the drug should be discontinued and appropriate medical therapy considered. If the cause of prolonged diarrhea remains unclear or continues after stopping entacapone, then further diagnostic investigations including colonoscopy and biopsies should be considered.

5.9 Rhabdomyolysis

Cases of severe rhabdomyolysis have been reported with entacapone when used in combination with carbidopa and levodopa. Severe prolonged motor activity including dyskinesia may possibly account for rhabdomyolysis. Most of the cases were manifested by myalgia and increased values of creatine phosphokinase (CPK) and myoglobin. Some of the reactions also included fever and/or alteration of consciousness. It is also possible that rhabdomyolysis may be a result of the syndrome described in Withdrawal-Emergent Hyperpyrexia and Confusion [see Warnings and Precautions (5.7)].

5.10 Interaction with Drugs Metabolized by COMT

Drugs known to be metabolized by COMT, such as isoproterenol, epinephrine, norepinephrine, dopamine, dobutamine, alpha-methyldopa, apomorphine, isoetherine, and bitolterol should be administered with caution in patients receiving entacapone regardless of the route of administration (including inhalation), as their interaction may result in increased heart rate, arrhythmia, and/or increased blood pressure.

5.11 Fibrotic Complications

Cases of retroperitoneal fibrosis, pulmonary infiltrates, pleural effusion, and pleural thickening have been reported in some patients treated with ergot derived dopaminergic agents. These complications may resolve when the drug is discontinued, but complete resolution does not always occur. Although these adverse reactions may be related to the ergoline structure of these compounds, a possible causal role of nonergot derived drugs (e.g., entacapone, levodopa), which increase dopaminergic activity, has also been considered. The expected incidence of fibrotic complications is so low that even if entacapone caused these complications at rates similar to those attributable to other dopaminergic therapies, it is unlikely that it would have been detected in a cohort of the size exposed to entacapone during its clinical development. Four cases of pulmonary fibrosis have been reported during clinical development of entacapone; 3 of these patients were also treated with pergolide and 1 with bromocriptine. The duration of treatment with entacapone ranged from 7 months to 17 months.

5.12 Peptic Ulcer Disease

As with levodopa, treatment with Stalevo may increase the possibility of upper gastrointestinal hemorrhage in patients with a history of peptic ulcer.

5.13 Hepatic Impairment

Patients with hepatic impairment should be treated with caution [see Clinical Pharmacology (12.3)]. As with levodopa, periodic evaluation of hepatic function is recommended during extended therapy.

5.14 Laboratory Tests

Abnormalities in laboratory tests may include elevations of liver function tests such as alkaline phosphatase, SGOT (AST), SGPT (ALT), lactic dehydrogenase, and bilirubin. Abnormalities in blood urea nitrogen and positive Coombs test have also been reported. Commonly, levels of blood urea nitrogen, creatinine, and uric acid are lower during administration of Stalevo than with levodopa.

Stalevo may cause a false-positive reaction for urinary ketone bodies when a test tape is used for determination of ketonuria. This reaction will not be altered by boiling the urine specimen. False-negative tests may result with the use of glucose-oxidase methods of testing for glucosuria.

Cases of falsely diagnosed pheochromocytoma in patients on carbidopa/levodopa therapy have been reported very rarely. Caution should be exercised when interpreting the plasma and urine levels of catecholamines and their metabolites in patients on carbidopa/levodopa therapy.

6 ADVERSE REACTIONS

The following adverse reactions are discussed in more detail in the Warnings and Precautions sections of labeling:

- Falling Asleep During Activities of Daily Living and Somnolence [see Warnings and Precautions (5.1)]
- Hypotension/Orthostatic Hypotension and Syncope [see Warnings and Precautions (5.2)]
- Dyskinesia [see Warnings and Precautions (5.3)]
- Depression and suicidality [see Warnings and Precautions (5.4)]
- Hallucinations/Psychotic-Like Behavior [see Warnings and Precautions (5.5)]
- Impulse Control and/or Compulsive Behaviors [see Warnings and Precautions (5.6)]
- Withdrawal-Emergent Hyperpyrexia and Confusion [see Warnings and Precautions (5.7)]
- Diarrhea and Colitis [see Warnings and Precautions (5.8)]
- Rhabdomyolysis [see Warnings and Precautions (5.9)]
- Peptic Ulcer Disease [see Warnings and Precautions (5.13)]

6.1 Clinical Trials Experience

Because clinical trials are conducted under widely varying conditions, the incidence of adverse reactions (number of unique patients experiencing an adverse reaction associated with treatment/total number of patients treated) observed in the clinical trials of a drug cannot be directly compared to the incidence of adverse reactions in the clinical trials of another drug and may not reflect the incidence of adverse reactions observed in clinical practice.

Entacapone

The most commonly observed adverse reactions (incidence at least 3% greater than placebo incidence) in the double-blind, carbidopa-levodopa-placebo-controlled trials of entacapone (N=1,003 patients) associated with the use of carbidopa-levodopa-entacapone alone and not seen at an equivalent frequency among the placebo-treated patients were: dyskinesia, diarrhea, nausea, hyperkinesia, abdominal pain, vomiting, dry mouth, and urine discoloration.

The treatment difference incidence for premature study discontinuation for entacapone with levodopa and dopa decarboxylase inhibitor in the double-blind, placebo-controlled trials was 5%. The treatment difference incidence for the most frequent causes of study discontinuation was 2% for diarrhea, and 1% for other specific adverse reactions including psychiatric reasons, dyskinesia/ hyperkinesia, nausea, or abdominal pain.

Adverse Reaction Incidence in Controlled Clinical Studies of Entacapone

Table 2 lists treatment emergent adverse reactions that occurred in at least 1% of patients treated with carbidopa/levodopa and 200 mg of entacapone who participated in the double-blind, placebo-controlled studies, and that were numerically more common in this group than in the carbidopa/levodopa plus placebo group. In these studies, either entacapone or placebo was added to carbidopa/levodopa (or benserazide/levodopa).

Table 2: Summary of Patients With Adverse Reactions After Start of Trial Drug Administration At Least 1% in Entacapone Group and Greater Than Placebo
SYSTEM ORGAN CLASS | Carbidopa/levodopa plus Entacapone | Carbidopa/levodopa plus Placebo
Adverse Reaction | (n=603) % of patients | (n=400) % of patients
SKIN AND APPENDAGES DISORDERS
Sweating Increased | 2 | 1
MUSCULOSKELETAL SYSTEM DISORDERS
Back Pain | 5 | 3
CENTRAL AND PERIPHERAL NERVOUS SYSTEM DISORDERS
Dyskinesia | 25 | 15
Hyperkinesia | 10 | 5
Hypokinesia | 9 | 8
Dizziness | 8 | 6
SPECIAL SENSES, OTHER DISORDERS
Taste Perversion | 1 | 0
PSYCHIATRIC DISORDERS
Anxiety | 2 | 1
Somnolence | 2 | 0
Agitation | 1 | 0
GASTROINTESTINAL SYSTEM DISORDERS
Nausea | 14 | 8
Diarrhea | 10 | 4
Abdominal Pain | 8 | 4
Constipation | 6 | 4
Vomiting | 4 | 1
Mouth Dry | 3 | 0
Dyspepsia | 2 | 1
Flatulence | 2 | 0
Gastritis | 1 | 0
Gastrointestinal Disorders NOS | 1 | 0
RESPIRATORY SYSTEM DISORDERS
Dyspnea | 3 | 1
PLATELET, BLEEDING AND CLOTTING DISORDERS
Purpura | 2 | 1
URINARY SYSTEM DISORDERS
Urine Discoloration | 10 | 0
BODY AS A WHOLE-GENERAL DISORDERS
Fatigue | 6 | 4
Asthenia | 2 | 1
RESISTANCE MECHANISM DISORDERS
Infection Bacterial | 1 | 0

6.2 Postmarketing Experience

The following spontaneous reports of adverse events temporally associated with entacapone or Stalevo have been identified since market introduction and are not listed in Table 2. Because these reactions are reported voluntarily from a population of unknown size, it is not always possible to reliably estimate their frequency or establish causal relationship to entacapone or Stalevo exposure.

Hepatitis with mainly cholestatic features has been reported.

Effects of Gender and Age on Adverse Reactions

No differences were noted in the rate of adverse reactions attributable to entacapone alone by age or gender.

7 DRUG INTERACTIONS

7.1 MAO Inhibitors

Patients receiving nonselective MAO inhibitors and carbidopa, levodopa and entacapone may be at risk of increased adrenergic tone. Therefore, the use of Stalevo is contraindicated in patients receiving nonselective MAO inhibitors [see Contraindications (4)].

7.2 Drugs Metabolized by Catechol-O-Methyltransferase (COMT)

Drugs known to be metabolized by COMT, such as isoproterenol, epinephrine, norepinephrine, dopamine, dobutamine, alpha-methyldopa, apomorphine, isoetherine, and bitolterol should be administered with caution in patients receiving entacapone regardless of the route of administration (including inhalation), as their interaction may result in increased heart rates, possibly arrhythmias, and excessive changes in blood pressure [see Warnings and Precautions (5.10)].

7.3 Antihypertensive Agents

Symptomatic postural hypotension has occurred when carbidopa/levodopa was added to the treatment of patients receiving antihypertensive drugs. When starting therapy with Stalevo, dosage adjustment of antihypertensive drug may be required.

7.4 Tricyclic Antidepressants

There have been reports of adverse reactions, including hypertension and dyskinesia, resulting from the concomitant use of tricyclic antidepressants and carbidopa/levodopa.

7.5 Dopamine D2 Receptor Antagonists

Dopamine D2 receptor antagonists (e.g., metoclopramide, phenothiazines, butyrophenones, risperidone) may reduce the therapeutic effects of levodopa.

7.6 Isoniazid

Isoniazid may reduce the therapeutic effects of levodopa, a dose increase may be necessary.

7.7 Phenytoin

The beneficial effects of levodopa in Parkinson's disease have been reported to be reversed by phenytoin. Patients taking phenytoin with carbidopa/levodopa should be carefully observed for loss of therapeutic response. Stalevo dosage should be increased as clinically needed in patients receiving phenytoin.

7.8 Papaverine

The beneficial effects of levodopa in Parkinson's disease have been reported to be reversed by papaverine. Patients taking papaverine with carbidopa/levodopa should be carefully observed for loss of therapeutic response. Stalevo dosage should be increased as clinically needed in patients receiving papaverine.

7.9 Iron Salts

Iron salts or multi vitamins containing iron salts should be coadministered with caution. Iron salts can form chelates with levodopa, carbidopa and entacapone and consequently reduce bioavailability of levodopa, carbidopa and entacapone.

7.10 Drugs Known to Interfere with Biliary Excretion, Glucuronidation, and Intestinal Beta-glucuronidase

As most entacapone excretion is via the bile, caution should be exercised when drugs known to interfere with biliary excretion, glucuronidation, and intestinal beta-glucuronidase are given concurrently with entacapone. These include probenecid, cholestyramine, and some antibiotics (e.g., erythromycin, rifampicin, ampicillin and chloramphenicol).

7.11 Drugs Metabolized via CYP2C9 (e.g., coumadin)

The dosage of Stalevo should be adjusted as clinically needed in patients using other drugs metabolized via CYP2C9. An interaction study in healthy volunteers, entacapone increased the AUC of R-warfarin on average by 18%, and the INR values on average by 13%. Cases of increased INR in patients concomitantly using warfarin have been reported during the post-approval use of entacapone. Thus, monitoring of INR is recommended when Stalevo treatment is initiated for patients receiving warfarin.

8 USE IN SPECIFIC POPULATIONS

8.1 Pregnancy

Risk Summary

There are no adequate data on the developmental risk associated with the use of Stalevo in pregnant women. In animals, administration of carbidopa-levodopa or entacapone during pregnancy was associated with developmental toxicity, including increased incidences of fetal malformations (see Data). The estimated background risk of major birth defects and miscarriage in the indicated population is unknown. In the U.S. general population, the estimated background risks of major birth defects and miscarriage in clinically recognized pregnancies are 2 to 4% and 15 to 20%, respectively.

Data

Animal data

In nonclinical studies in which carbidopa-levodopa was administered to pregnant animals, increased incidences of visceral and skeletal malformations were observed in rabbits at all doses and ratios of carbidopa-levodopa tested, which ranged from 10 times (carbidopa)-5 times (levodopa) to 20 times (carbidopa)-10 times (levodopa) the maximum recommended human dose (MRHD) of 1,600 mg/day. In rats, there was a decrease in the number of live pups delivered by dams receiving approximately two times (carbidopa)-five times (levodopa) the MRHD throughout organogenesis. No effects on malformation frequencies were observed in mice receiving up to 20 times the MRHD of carbidopa-levodopa.

In embryo-fetal development studies of entacapone, pregnant animals received doses of up to 1,000 mg/kg/day (rats) or 300 mg/kg/day (rabbits) throughout organogenesis. Increased incidences of fetal variations were evident in litters from rats treated with the highest dose, in the absence of overt signs of maternal toxicity. The maternal plasma entacapone exposure (AUC) associated with this dose was approximately 34 times that in humans at the MRHD. Increased frequencies of abortions and late/total resorptions and decreased fetal weights were observed in the litters of rabbits treated with maternally toxic doses of 100 mg/kg/day (plasma AUCs less than that in humans at the MRHD) or greater. There were no increases in malformation rates in these studies.

When entacapone was administered to female rats prior to mating and during early gestation, an increased incidence of fetal eye anomalies (macrophthalmia, microphthalmia, anophthalmia) was observed in the litters of dams treated with doses of 160 mg/kg/day (plasma AUCs seven times that in humans at the MRHD) or greater, in the absence of maternal toxicity. Administration of up to 700 mg/kg/day (plasma AUCs 28 times that in humans at the MRHD) to rats during the latter part of gestation and throughout lactation produced no evidence of developmental impairment in the offspring.

8.2 Lactation

Risk Summary

Levodopa has been detected in human milk after administration of carbidopa-levodopa. There are no data on the presence of entacapone or carbidopa in human milk, the effects of levodopa, carbidopa, or entacapone on the breastfed infant, or the effects on milk production. However, inhibition of lactation may occur because levodopa decreases secretion of prolactin [see Clinical Pharmacology (12.6)]. Carbidopa and entacapone are excreted in rat milk. In lactating rat, oral administration of radiolabeled entacapone resulted in levels of entacapone and/or metabolites in milk up to 2 to 3 times that in plasma.

The developmental and health benefits of breastfeeding should be considered along with the mother's clinical need for Stalevo and any potential adverse effects on the breastfed infant from Stalevo or from the underlying maternal condition.

8.4 Pediatric Use

Safety and effectiveness in pediatric patients have not been established.

8.5 Geriatric Use

Of the total number of subjects in clinical studies of Stalevo, 43.8% were 65 years old and over, while 7.2% were 75 years old and over. No overall differences in safety or effectiveness were observed between these subjects and younger subjects, and other reported clinical experience has not identified differences in responses between the elderly and younger patients; however, greater sensitivity of some older individuals cannot be excluded.

Stalevo tablets have not been studied in Parkinson's disease patients or in healthy volunteers older than 75 years [see Clinical Pharmacology (12.3)].

8.6 Renal Impairment

Renal impairment does not affect pharmacokinetics of entacapone. There are no studies on the pharmacokinetics of levodopa and carbidopa in patients with renal impairment [see Clinical Pharmacology (12.3)].

8.7 Hepatic Impairment or Biliary Obstruction

There are no studies on the pharmacokinetics of carbidopa and levodopa in patients with hepatic impairment. Stalevo should be administered cautiously to patients with biliary obstruction or hepatic disease since biliary excretion appears to be the major route of excretion of entacapone and hepatic impairment had a significant effect on the pharmacokinetics of entacapone when 200 mg entacapone was administered alone [see Clinical Pharmacology (12.3)].

10 OVERDOSAGE

10.1 Signs and Symptoms of Overdosage

There are very few cases of overdose with levodopa reported in the published literature. Based on the available information, the acute symptoms of levodopa and dopa decarboxylase inhibitor overdose can be expected to arise from dopaminergic overstimulation. Doses of a few grams may result in CNS disturbances, with an increasing likelihood of cardiovascular disturbance (e.g., hypotension, tachycardia) and more severe psychiatric problems at higher doses. An isolated report of rhabdomyolysis and another of transient renal insufficiency suggest that levodopa overdose may give rise to systemic complications, secondary to dopaminergic overstimulation.

COMT inhibition by entacapone treatment is dose-dependent. A massive overdose of entacapone may theoretically produce a 100% inhibition of the COMT enzyme in people, thereby preventing the O-methylation of endogenous and exogenous catechols.

In clinical trials, the highest single dose of entacapone administered to humans was 800 mg, resulting in a plasma concentration of 14.1 mcg per mL. The highest daily dose given to humans was 2,400 mg, administered in one study as 400 mg six times daily with carbidopa/levodopa for 14 days in 15 Parkinson's disease patients, and in another study as 800 mg three times daily for 7 days in 8 healthy volunteers. At this daily dose, the peak plasma concentrations of entacapone averaged 2.0 mcg per mL (at 45 min, compared to 1.0 mcg per mL and 1.2 mcg per mL with 200 mg entacapone at 45 min.). Abdominal pain and loose stools were the most commonly observed adverse events during this study. Daily doses as high as 2,000 mg entacapone have been administered as 200 mg 10 times daily with carbidopa/levodopa or benserazide/levodopa for at least 1 year in 10 patients, for at least 2 years in 8 patients and for at least 3 years in 7 patients. Overall, however, clinical experience with daily doses above 1,600 mg is limited.

10.2 Management of Overdosage

Hospitalization is advised, and general supportive measures should be employed, along with immediate gastric lavage and repeated doses of charcoal over time. This may hasten the elimination of entacapone in particular, by decreasing its absorption and reabsorption from the GI tract. Intravenous fluids should be administered judiciously and an adequate airway maintained.

Respiratory, circulatory and renal function should be monitored and appropriate supportive measures employed. Electrocardiographic monitoring should be instituted and the patient carefully observed for the development of arrhythmias; if required, appropriate antiarrhythmic therapy should be given. The possibility that the patient may have taken other drugs, increasing the risk of drug interactions (especially catechol-structured drugs) should be taken into consideration. To date, no experience has been reported with dialysis; hence, its value in overdosage is not known. Hemodialysis or hemoperfusion is unlikely to reduce entacapone levels due to its high binding to plasma proteins.

Pyridoxine is not effective in reversing the actions of Stalevo.

11 DESCRIPTION

Stalevo is a combination of carbidopa, levodopa, and entacapone for the treatment of Parkinson's disease.

Carbidopa, an inhibitor of aromatic amino acid decarboxylation, is a white, crystalline compound, slightly soluble in water, with a molecular weight of 244.3. It is designated chemically as (-)-L-(α-hydrazino-(α-methyl-β-(3,4-dihydroxybenzene) propanoic acid monohydrate. Its empirical formula is C10H14N2O4∙H2O, and its structural formula is:

Tablet content is expressed in terms of anhydrous carbidopa, which has a molecular weight of 226.3.

Levodopa, an aromatic amino acid, is a white, crystalline compound, slightly soluble in water, with a molecular weight of 197.2. It is designated chemically as (-)-L-α-amino-β-(3,4-dihydroxybenzene) propanoic acid. Its empirical formula is C9H11NO4, and its structural formula is:

Entacapone, a COMT inhibitor, is a nitro-catechol-structured compound with a molecular weight of 305.3. The chemical name of entacapone is (E)-2-cyano-3-(3,4-dihydroxy-5-nitrophenyl)-N,N-diethyl-2-propenamide. Its empirical formula is C14H15N3O5 and its structural formula is:

Stalevo is supplied as tablets in 6 strengths:

Stalevo 50:12.5 mg of carbidopa, 50 mg of levodopa and 200 mg of entacapone

Stalevo 75: 18.75 mg of carbidopa, 75 mg of levodopa and 200 mg of entacapone

Stalevo 100: 25 mg of carbidopa, 100 mg of levodopa and 200 mg of entacapone

Stalevo125: 31.25 mg of carbidopa, 125 mg of levodopa and 200 mg of entacapone

Stalevo 150: 37.5 mg of carbidopa, 150 mg of levodopa and 200 mg of entacapone

Stalevo 200: 50 mg of carbidopa, 200 mg of levodopa and 200 mg of entacapone

Inactive Ingredients: corn starch, croscarmellose sodium, glycerol 85%, hypromellose, magnesium stearate, mannitol, polysorbate 80, povidone, sucrose, red iron oxide, and titanium dioxide. Stalevo 50, Stalevo 100, and Stalevo 150 also contain yellow iron oxide.

12 CLINICAL PHARMACOLOGY

12.1 Mechanism of Action

Levodopa

Current evidence indicates that symptoms of Parkinson's disease are related to depletion of dopamine in the corpus striatum. Administration of dopamine is ineffective in the treatment of Parkinson's disease because it does not cross the blood-brain barrier. However, levodopa the metabolic precursor of dopamine, does cross the blood-brain barrier, and is presumably converted to dopamine in the brain. This is thought to be the mechanism whereby levodopa relieves the symptoms of Parkinson's disease.

Carbidopa

When levodopa is administered orally, it is rapidly decarboxylated to dopamine in extracerebral tissues so that only a small portion of a given dose is transported unchanged to the central nervous system. Carbidopa inhibits the decarboxylation of peripheral levodopa, making more levodopa available for delivery to the brain.

Entacapone

Entacapone is a selective and reversible inhibitor of catechol-O-methyltransferase (COMT).

COMT catalyzes the transfer of the methyl group of S-adenosyl-L-methionine to the phenolic group of substrates that contain a catechol structure. Physiological substrates of COMT include DOPA, catecholamines (dopamine, norepinephrine, and epinephrine) and their hydroxylated metabolites. When decarboxylation of levodopa is prevented by carbidopa, COMT becomes the major metabolizing enzyme for levodopa, catalyzing its metabolism to 3-methoxy-4-hydroxy-L-phenylalanine (3-OMD).

12.3 Pharmacokinetics

The pharmacokinetics of Stalevo tablets has been studied in healthy subjects (age 45 years to 75 years). Overall, following administration of corresponding doses of levodopa, carbidopa and entacapone as Stalevo or as carbidopa and levodopa product plus Comtan (entacapone) tablets, the mean plasma concentrations of levodopa, carbidopa, and entacapone are comparable.

Absorption and Distribution

Both levodopa and entacapone are rapidly absorbed and eliminated, and their distribution volume is moderately small. Carbidopa is absorbed and eliminated slightly more slowly compared with levodopa and entacapone. There are substantial inter- and intra-individual variations in the absorption of levodopa, carbidopa and entacapone, particularly concerning its Cmax.

The food-effect on the Stalevo tablet has not been evaluated. Because levodopa competes with certain amino acids for transport across the gut wall, the absorption of levodopa may be impaired in some patients after eating a high protein meal. Meals rich in large neutral amino acids may delay and reduce the absorption of levodopa [see Patient Counseling Information (17)].

Levodopa

The pharmacokinetic properties of levodopa following the administration of single-dose Stalevo (carbidopa, levodopa and entacapone) tablets are summarized in Table 3.

Table 3: Pharmacokinetic Characteristics of Levodopa with Different Tablet Strengths of Stalevo (mean ± SD)
 | AUC0-∞ | Cmax | Tmax
Tablet Strength | (nanogram∙h per mL) | (nanogram per mL) | (h)
12.5 mg per 50 mg per 200 mg | 1,040 ± 314 | 470 ± 154 | 1.1 ± 0.5
25 mg per 100 mg per 200 mg | 2,910 ± 715 | 975 ± 247 | 1.4 ± 0.6
37.5 mg per 150 mg per 200 mg | 3,770 ± 1,120 | 1,270 ± 329 | 1.5 ± 0.9
50 mg per 200 mg per 200 mg | 6,115 ± 1,536 | 1,859 ± 455 | 1.76 ± 0.7

Levodopa is bound to plasma protein only to a minor extent (about 10% to 30%).

Carbidopa

Following administration of Stalevo as a single dose to healthy male and female subjects, the peak concentration of carbidopa was reached within 2.5 hours to 3.4 hours on average. The mean Cmax ranged from about 40 nanogram per mL to 225 nanogram per mL and the mean AUC from 170 nanogram∙h per mL to 1,200 nanogram∙h per mL, with different Stalevo strengths providing 12.5 mg, 25 mg, 37.5 mg, or 50 mg of carbidopa.

Carbidopa is approximately 36% bound to plasma protein.

Entacapone

Following administration of Stalevo as a single dose to healthy male and female subjects, the peak concentration of entacapone in plasma was reached within 0.8 hour to 1.2 hours on average. The mean Cmax of entacapone was about 1,200 nanogram per mL to 1,500 nanogram per mL and the AUC 1,250 nanogram∙h per mL to 1,750 nanagram∙h per mL after administration of different Stalevo strengths all providing 200 mg of entacapone.

The plasma protein binding of entacapone is 98% over the concentration range of 0.4 mcg per mL to 50 mcg per mL. Entacapone binds mainly to serum albumin.

Metabolism and Elimination

Levodopa

The elimination half-life of levodopa, the active moiety of antiparkinsonian activity, was 1.7 hours (range 1.1 hours to 3.2 hours).

Levodopa is extensively metabolized to various metabolites. Two major pathways are decarboxylation by dopa decarboxylase (DDC) and O-methylation by COMT.

Carbidopa

The elimination half-life of carbidopa was on average 1.6 hours to 2 hours (range 0.7 hour to 4.0 hours).

Carbidopa is metabolized to two main metabolites (α-methyl-3-methoxy-4-hydroxyphenylpropionic acid and α-methyl-3,4-dihydroxyphenylpropionic acid). These 2 metabolites are primarily eliminated in the urine unchanged or as glucuronide conjugates. Unchanged carbidopa accounts for 30% of the total urinary excretion.

Entacapone

The elimination half-life of entacapone was on average 0.8 hour to 1 hour (0.3 hour to 4.5 hours).

Entacapone is almost completely metabolized prior to excretion with only a very small amount (0.2% of dose) found unchanged in urine. The main metabolic pathway is isomerization to the cis-isomer, the only active metabolite. Entacapone and the cis-isomer are eliminated in the urine as glucuronide conjugates. The glucuronides account for 95% of all urinary metabolites (70% as parent and 25% as cis-isomer glucuronides). The glucuronide conjugate of the cis-isomer is inactive. After oral administration of a ^14C-labeled dose of entacapone, 10% of labeled parent and metabolite is excreted in urine and 90% in feces.

Due to short elimination half-lives, no true accumulation of levodopa or entacapone occurs when they are administered repeatedly.

Renal Impairment

Entacapone

The pharmacokinetics of entacapone have been investigated after a single 200 mg entacapone dose in subjects with normal, moderate, and severely impaired renal functions, without levodopa and dopa decarboxylase inhibitor coadministration. No significant effects of renal function on the pharmacokinetics of entacapone were found.

Levodopa and carbidopa

No studies on the pharmacokinetics of levodopa and carbidopa in patients with renal impairment.

Hepatic Impairment

Entacapone

Hepatic impairment had a significant effect on the pharmacokinetics of entacapone when 200 mg entacapone was administered alone. A single 200 mg dose of entacapone, without levodopa and dopa decarboxylase inhibitor coadministration, showed approximately 2-fold higher AUC and Cmax values in patients with a history of alcoholism and hepatic impairment (n=10) compared to normal subjects (n=10). All patients had biopsy-proven liver cirrhosis caused by alcohol. According to Child-Pugh grading 7 patients with liver disease had mild hepatic impairment and 3 patients had moderate hepatic impairment. As only about 10% of the entacapone dose is excreted in urine, as parent compound and conjugated glucuronide, biliary excretion appears to be the major route of excretion of this drug. Stalevo should be administered with care to patients with biliary obstruction or hepatic disease.

Levodopa and carbidopa

There are no studies on the pharmacokinetics of levodopa and carbidopa in patients with hepatic impairment.

Geriatric Use

In the pharmacokinetics studies conducted in healthy volunteers following a single dose of carbidopa-, levodopa- and entacapone (as Stalevo or as separate carbidopa/levodopa and Comtan tablets):

Levodopa

The AUC of levodopa is significantly (on average 10% to 20%) higher in elderly (60 years to 75 years) than younger subjects (45 years to 60 years). There is no significant difference in the Cmax of levodopa between younger (45 years to 60 years) and elderly subjects (60 years to 75 years).

Carbidopa

There is no significant difference in the Cmax and AUC of carbidopa, between younger (45 years to 60 years) and elderly subjects (60 years to 75 years).

Entacapone

The AUC of entacapone is significantly (on average, 15%) higher in elderly (60 years to 75 years) than younger subjects (45 years to 60 years). There is no significant difference in the Cmax of entacapone between younger (45 years to 60 years) and elderly subjects (60 years to 75 years).

Gender

Pharmacokinetics following a single dose of carbidopa, levodopa and entacapone together, either as Stalevo or as separate carbidopa/levodopa and Comtan tablets in healthy volunteers (age range 45 years to 74 years):

Levodopa

The plasma exposure (AUC and Cmax) of levodopa is significantly higher in females than males (on average, 40% for AUC and 30% for Cmax). These differences are primarily explained by body weight. Other published literature showed significant gender effect (higher concentrations in females) even after correction for body weight.

Carbidopa

There is no gender difference in the pharmacokinetics of carbidopa.

Entacapone

There is no gender difference in the pharmacokinetics of entacapone.

Drug Interaction Studies

Drug Metabolized by COMT

When a single 400 mg dose of entacapone was given together with intravenous isoprenaline (isoproterenol) and epinephrine without coadministered levodopa and dopa decarboxylase inhibitor, the overall mean maximal changes in heart rate during infusion were about 50% and 80% higher than with placebo, for isoprenaline and epinephrine, respectively.

Drugs known to be metabolized by COMT should be administered with caution in patients receiving entacapone regardless of the route of administration [see Drug Interactions (7.2)].

Drugs Metabolized via CYP2C9

Due to its affinity to CYP2C9 in vitro, entacapone may potentially interfere with medicinal products with metabolism dependent on this isoenzyme. In an interaction study in healthy volunteers, entacapone increased the AUC of R-warfarin on average by 18%, and the INR values increased on average by 13% [see Drug Interactions (7.11)].

12.6 Hormone Levels

Of the ingredients in Stalevo, levodopa is known to depress prolactin secretion and increase growth hormone levels.

13 NONCLINICAL TOXICOLOGY

13.1 Carcinogenesis, Mutagenesis, Impairment of Fertility

Carcinogenesis

In rats, oral administration of carbidopa-levodopa for 2 years resulted in no evidence of carcinogenicity at doses of approximately 2 times (carbidopa)-4 times (levodopa) the maximum recommended human dose (MRHD).

Two-year carcinogenicity studies of entacapone were conducted in mice and rats. In mice, no increase in tumors was observed at oral doses of 100, 200 and 400 mg/kg/day. At the highest dose tested, plasma exposures (AUC) were 4 times higher than that in humans at the maximum recommended daily dose (MRDD) of 1,600 mg. In rats administered oral doses of 20, 90, or 400 mg/kg/day, an increased incidence of renal tubular adenomas and carcinomas was observed in males at the highest dose tested. Plasma AUCs at the higher dose not associated with increased renal tumors (90 mg/kg/day) were approximately 5 times that in humans at the MRDD of entacapone.

The carcinogenic potential of entacapone administered in combination with carbidopa-levodopa has not been evaluated.

Mutagenesis

Carbidopa was mutagenic in the in vitro bacterial reverse mutation (Ames) assay in the presence and absence of metabolic activation, and in the in vitro mouse lymphoma thymidine kinase (tk) assay in the absence of metabolic activation. Carbidopa was negative in the in vivo mouse micronucleus assay.

Entacapone was mutagenic and clastogenic in the in vitro mouse lymphoma tk assay in the presence and absence of metabolic activation, and was clastogenic in cultured human lymphocytes in the presence of metabolic activation. Entacapone, either alone or in combination with carbidopa-levodopa, was negative in the in vivo mouse micronucleus and in the Ames assays.

Impairment of Fertility

In reproduction studies, no effects on fertility were found in rats receiving carbidopa-levodopa at doses of approximately 2 times (carbidopa)-4 times (levodopa) the MRHD.

In rats treated orally with entacapone (up to 700 mg/kg/day), no effects on fertility or general reproductive performance were observed. Plasma exposures (AUC) at the highest dose tested were approximately 30 times that in humans at the MRHD of entacapone. Delayed mating was evident in females at the highest dose tested.

14 CLINICAL STUDIES

The effectiveness of entacapone as an adjunct to levodopa in the treatment of Parkinson's disease was established in three 24-week multicenter, randomized, double-blind, placebo-controlled studies in patients with Parkinson's disease. In 2 of these studies (Studies 1 and 2), the patients' disease was "fluctuating", i.e., was characterized by documented periods of "On" (periods of relatively good functioning) and "Off" (periods of relatively poor functioning), despite optimum levodopa therapy. There was also a withdrawal period following 6 months of treatment. In the third trial patients were not required to have been experiencing fluctuations. Prior to the controlled part of these studies, patients were stabilized on levodopa for 2 weeks to 4 weeks.

There is limited experience using entacapone in patients who do not experience fluctuations.

In Studies 1 and 2, patients were randomized to receive placebo or entacapone 200 mg administered concomitantly with each dose of carbidopa/levodopa (up to 10 times daily, but patients averaged 4 doses to 6 doses per day). The double-blind portion of both studies was 6 months long. Patients periodically recorded the time spent in the "On" and "Off" states in home diaries throughout the duration of the trial. In one study, conducted in the Nordic countries, the primary outcome measure was the total mean time spent in the "On" state during an 18 hour diary recorded day (6 a.m. to midnight). In the other study, the primary outcome measure was the proportion of awake time spent over 24 hours in the "On" state.

In addition to the primary outcome measure, the amount of time spent in the "Off" state was evaluated, and patients were also evaluated by subparts of the Unified Parkinson's Disease Rating Scale (UPDRS), a frequently used multi-item rating scale intended to assess mentation (Part I), activities of daily living (Part II), motor function (Part III), complications of therapy (Part IV), and disease staging (Part V and VI); an investigator's and patient's global assessment of clinical condition, a 7-point subjective scale designed to assess global functioning in Parkinson's disease; and the change in daily carbidopa/levodopa dose.

In Study 1, 171 patients were randomized in 16 centers in Finland, Norway, Sweden, and Denmark (Study 1), all of whom received concomitant levodopa plus dopa decarboxylase inhibitor (either carbidopa/levodopa or benserazide/levodopa). In Study 2, 205 patients were randomized in 17 centers in North America (US and Canada); all patients received concomitant carbidopa/levodopa.

The following tables (Table 4 and Table 5) display the results of these two studies:

Table 4: Efficacy Results of Study 1
Primary Measure from Home Diary (from an 18-hour Diary Day)
 | Baseline | Change from Baseline at Month 6 [Mean; the month 6 values represent the average of weeks 8, 16, and 24, by protocol-defined outcome measure.] | p-value vs. placebo
Hours of Awake Time "On"
Placebo | 9.2 | +0.1 | –
Entacapone | 9.3 | +1.5 | less than 0.001
Duration of "On" Time After First AM Dose (Hrs)
Placebo | 2.2 | 0.0 | –
Entacapone | 2.1 | +0.2 | less than 0.05
Secondary Measures from Home Diary (from an 18-hour Diary Day) [P values for Secondary Measures are nominal P values without any adjustment for multiplicity.]
Hours of Awake Time "Off"
Placebo | 5.3 | 0.0 | –
Entacapone | 5.5 | -1.3 | less than 0.001
Proportion of Awake Time "On" [Not an endpoint for this study but primary endpoint in the North American Study.] (%)
Placebo | 63.8 | +0.6 | –
Entacapone | 62.7 | +9.3 | less than 0.001
Levodopa Total Daily Dose (mg)
Placebo | 705 | +14 | –
Entacapone | 701 | -87 | less than 0.001
Frequency of Levodopa Daily Intakes
Placebo | 6.1 | +0.1 | –
Entacapone | 6.2 | - 0.4 | less than 0.001
Other Secondary Measures
 | Baseline | Change from Baseline at Month 6 | p-value vs. placebo
Investigator's Global (overall) % Improved [At least one category change at endpoint.]
Placebo | – | 28 | –
Entacapone | – | 56 | less than 0.01
Patient's Global (overall) % Improved§
Placebo | – | 22 | –
Entacapone | – | 39 | N.S. [Not significant.]
UPDRS Total
Placebo | 37.4 | -1.1 | –
Entacapone | 38.5 | -4.8 | less than 0.01
UPDRS Motor
Placebo | 24.6 | -0.7 | –
Entacapone | 25.5 | -3.3 | less than 0.05
UPDRS ADL
Placebo | 11.0 | -0.4 | –
Entacapone | 11.2 | -1.8 | less than 0.05

Table 5: Efficacy Results of Study 2
Primary Measure from Home Diary (for a 24-hour Diary Day)
 | Baseline | Change from Baseline at Month 6 [Mean; the month 6 values represent the average of weeks 8, 16, and 24, by protocol-defined outcome measure.] | p-value vs. placebo
Percent of Awake Time "On"
Placebo | 60.8 | +2.0 | –
Entacapone | 60.0 | +6.7 | less than 0.05
Secondary Measures from Home Diary (for a 24-hour Diary Day) [P values for Secondary Measures are nominal P values without any adjustment for multiplicity.]
Hours of Awake Time "Off"
Placebo | 6.6 | -0.3 | –
Entacapone | 6.8 | -1.2 | less than 0.01
Hours of Awake Time "On"
Placebo | 10.3 | +0.4 | –
Entacapone | 10.2 | +1.0 | N.S. [Not significant.]
Levodopa Total Daily Dose (mg)
Placebo | 758 | +19 | –
Entacapone | 804 | -93 | less than 0.001
Frequency of Levodopa Daily Intakes
Placebo | 6.0 | +0.2 | –
Entacapone | 6.2 | 0.0 | N.S. ‡
Other Secondary Measures†
 | Baseline | Change from Baseline at Month 6 | p-value vs. placebo
Investigator's Global (overall) % Improved [At least one category change at endpoint.]
Placebo | – | 21 | –
Entacapone | – | 34 | less than 0.05
Patient's Global (overall) % Improved§
Placebo | – | 20 | –
Entacapone | – | 31 | less than 0.05
UPDRS Total [Score change at endpoint similarly to the Nordic Study.]
Placebo | 35.6 | +2.8 | –
Entacapone | 35.1 | -0.6 | less than 0.05
UPDRS Motor ¶
Placebo | 22.6 | +1.2 | –
Entacapone | 22.0 | -0.9 | less than 0.05
UPDRS ADL ¶
Placebo | 11.7 | +1.1 | –
Entacapone | 11.9 | 0.0 | less than 0.05

Effects on "On" time did not differ by age, sex, weight, disease severity at baseline, levodopa dose and concurrent treatment with dopamine agonists or selegiline.

Withdrawal of entacapone:

In Study 2, abrupt withdrawal of entacapone, without alteration of the dose of carbidopa/levodopa, resulted in a significant worsening of fluctuations, compared to placebo. In some cases, symptoms were slightly worse than at baseline, but returned to approximately baseline severity within 2 weeks following levodopa dose increase on average by 80 mg. In Study 1, similarly, a significant worsening of parkinsonian symptoms was observed after entacapone withdrawal, as assessed 2 weeks after drug withdrawal. At this phase, the symptoms were approximately at baseline severity following levodopa dose increase by about 50 mg.

In the third placebo-controlled trial (Study 3), a total of 301 patients were randomized in 32 centers in Germany and Austria. In this trial, as in the other 2 studies, entacapone 200 mg was administered with each dose of levodopa and dopa decarboxylase inhibitor (up to 10 times daily) and UPDRS Parts II and III and total daily "On" time were the primary measures of effectiveness. Results for the primary measures, as well as for some secondary measures are presented in Table 6.

Table 6: Efficacy Results of Study 3
Primary Measures
 | Baseline | Change from Baseline at Month 6 | p-value vs. placebo (LOCF)
UPDRS ADL [Total population; score change at endpoint.]
Placebo | 12.0 | +0.5 | –
Entacapone | 12.4 | -0.4 | less than 0.05
UPDRS Motor*
Placebo | 24.1 | +0.1 | –
Entacapone | 24.9 | -2.5 | less than 0.05
Hours of Awake Time "On" (Home Diary) [Fluctuating population, with 5 doses to 10 doses; score change at endpoint.]
Placebo | 10.1 | +0.5 | –
Entacapone | 10.2 | +1.1 | N.S. [Not significant.]
Secondary Measures [P values for Secondary Measures are nominal P values without any adjustment for multiplicity.]
 | Baseline | Change from Baseline at Month 6 | p-value vs. placebo
UPDRS Total *
Placebo | 37.7 | +0.6 | –
Entacapone | 39.0 | -3.4 | less than 0.05
Percent of Awake Time "On" (Home Diary) **
Placebo | 59.8 | +3.5 | –
Entacapone | 62.0 | +6.5 | N.S. ‡
Hours of Awake Time "Off" (Home Diary)
Placebo | 6.8 | -0.6 | –
Entacapone | 6.3 | -1.2 | 0.07
Levodopa Total Daily Dose (mg)*
Placebo | 572 | +4 | –
Entacapone | 566 | -35 | N.S.
Frequency of Levodopa Daily Intake*
Placebo | 5.6 | +0.2 | –
Entacapone | 5.4 | 0.0 | less than 0.01
Global (overall) % Improved [Total population; at least one category change at endpoint.]
Placebo | – | 34 | –
Entacapone | – | 38 | N.S. ‡

16 HOW SUPPLIED/STORAGE AND HANDLING

Stalevo (carbidopa, levodopa and entacapone) is supplied as film-coated tablets for oral administration in the following six strengths:

Stalevo 50 film-coated tablets containing 12.5 mg of carbidopa, 50 mg of levodopa, and 200 mg of entacapone.

The round, bi-convex shaped tablets are brownish- or greyish-red, unscored, and embossed "LCE 50" on one side.

 | HDPE bottle of 100 tablets | NDC 52427‑805‑01

Stalevo 75 film-coated tablets containing 18.75 mg of carbidopa, 75 mg of levodopa, and 200 mg of entacapone.

The oval-shaped tablets are light brownish red, unscored and embossed with code "LCE 75" on one side.

 | HDPE bottle of 100 tablets | NDC 52427‑809‑01

Stalevo 100 film-coated tablets containing 25 mg of carbidopa, 100 mg of levodopa, and 200 mg of entacapone.

The oval-shaped tablets are brownish- or greyish-red, unscored, and embossed "LCE 100" on one side.

 | HDPE bottle of 100 tablets | NDC 52427‑816‑01

Stalevo 125 film-coated tablets containing 31.25 mg of carbidopa, 125 mg of levodopa, and 200 mg of entacapone.

The oval-shaped tablets are light brownish red, unscored and embossed with code "LCE 125" on one side.

 | HDPE bottle of 100 tablets | NDC 52427‑827‑01

Stalevo 150 film-coated tablets containing 37.5 mg of carbidopa, 150 mg of levodopa, and 200 mg of entacapone.

The elongated-ellipse shaped tablets are brownish- or greyish-red, unscored, and embossed "LCE 150" on one side.

 | HDPE bottle of 100 tablets | NDC 52427‑834‑01

Stalevo 200 film-coated tablets containing 50 mg of carbidopa, 200 mg of levodopa, and 200 mg of entacapone.

The oval shaped tablets are dark brownish red, unscored, and embossed "LCE 200" on one side.

 | HDPE bottle of 100 tablets | NDC 52427‑842‑01

STORAGE AND HANDLING

Store at 25°C (77°F); excursions permitted to 15°C to 30°C (59°F to 86°F).

[See USP Controlled Room Temperature.]

Dispense in tight container (USP).

17 PATIENT COUNSELING INFORMATION

Falling Asleep During Activities of Daily Living and Somnolence

Advise patients about the potential for sedating effects associated with Stalevo including somnolence and the possibility of falling asleep while engaged in activities of daily living. Because somnolence can be a frequent adverse reaction with potentially serious consequences, patients should not drive a motor vehicle, operate heavy machinery or engage in other potentially dangerous activities until they have gained sufficient experience with Stalevo to determine whether or not it affects their mental and/or motor performance adversely [see Warnings and Precautions (5.1)]. Advise patients that if increased somnolence or episodes of falling asleep during activities of daily living (e.g., conversations, eating, driving a motor vehicle, etc.) are experienced at any time during treatment, they should not drive or participate in potentially dangerous activities until they have contacted their physician.

Advise patients to speak with their health care prescriber before taking alcohol, sedating medications, or other CNS depressants (e.g., benzodiazepines, antipsychotics, antidepressants, etc.) because of the possible additive effects in combination with Stalevo.

Hypotension, Orthostatic Hypotension and Syncope

Advise patients that they may develop symptomatic (or asymptomatic) postural (orthostatic) hypotension or non-orthostatic hypotension while taking Stalevo. Hypotension/orthostatic hypotension may occur more frequently during initial therapy. Patients should not rise rapidly after sitting or lying down, especially if they have been doing so for prolonged periods and especially at the initiation of treatment with Stalevo.

Advise patients about the potential for syncope in patients using dopamine agonists. For this reason, inform patients about the possibility of syncope while taking Stalevo [see Warnings and Precautions (5.2)].

Dyskinesias

Inform patients that Stalevo may cause and/or exacerbate pre-existing dyskinesias [see Warnings and Precautions (5.3)].

Hallucinations and/or Psychotic-Like Behavior

Inform patients that hallucinations and other psychotic-like behavior can occur while taking Stalevo [see Warnings and Precautions (5.5)].

Impulse Control and/or Compulsive Behaviors

Advise patients that they may experience impulse control and/or compulsive behaviors while taking one or more of the medications used for the treatment of Parkinson's disease, including Stalevo. Ask patients about the development of new or increased gambling urges, sexual urges, urges for uncontrolled spending, or other intense urges while being treated with Stalevo. Advise patients to inform their physician or health care provider if they experience new or increased gambling urges, increased sexual urges or other intense urges while taking Stalevo. Physicians should consider dose reduction or stopping the medication if a patient develops such urges while taking Stalevo [see Warnings and Precautions (5.6)].

Withdrawal-Emergent Hyperpyrexia and Confusion

Advise patients that they may develop fever and confusion as part of a syndrome resembling NMS and possibly with other clinical features (e.g., muscle rigidity, autonomic dysfunction, hyper- or hypotension, etc.). This fever and confusion syndrome may particularly occur with dose reductions or withdrawal of Stalevo but may also develop after initiation of treatment. Advise patients to contact their healthcare provider if they wish to discontinue or decrease the dose of Stalevo and to contact a health care provider if they develop fever and confusion [see Warnings and Precautions (5.7)].

Diarrhea and Colitis

Inform the patients that diarrhea may occur with Stalevo and it may have a delayed onset. Sometimes prolonged diarrhea may be caused by colitis (inflammation of the large intestine). Patients with diarrhea should drink fluids to maintain adequate hydration and monitor for weight loss. If diarrhea associated with Stalevo is prolonged, discontinuing the drug is expected to lead to resolution. If diarrhea continues after stopping Stalevo, further diagnostic investigations may be needed. In some cases, diarrhea may be associated with colitis [see Warnings and Precautions (5.8)].

Rhabdomyolysis

Advise patients that they may develop rhabdomyolysis and myalgia if they experience prolonged motor activity including dyskinesia. This event may also be associated with fever and confusion [see Warnings and Precautions (5.9)].

Nausea and Vomiting

Inform patients that Stalevo may cause nausea and vomiting may occur more frequently during initial therapy and may require dose adjustment.

Instructions for Use

Instruct patients to take Stalevo only as prescribed. Instruct patients to only take a single tablet of Stalevo at each dosing interval. Instruct patients not to take multiple tablets or additional portions of tablets to achieve a higher dose of levodopa. Advise patients not to split, crush, or chew Stalevo.

Inform the patient that Stalevo is a formulation of carbidopa/levodopa combined with entacapone that is designed to begin release of ingredients within 30 minutes after ingestion. It is important that Stalevo be taken at regular intervals according to the schedule outlined by the physician. Caution the patient not to change the prescribed dosage regimen and not to add any additional antiparkinsonian medications, including other carbidopa/levodopa preparations, without first consulting the physician.

Advise patients that "off" episodes ("wearing-off" of drug effect) occur at the end of the dosing interval but unpredictable "off" episodes may occur at any time. Advise the patient to notify a health care provider for possible treatment adjustments if such response poses a problem to the patient's everyday life.

Advise patients that dark coloration (red, brown, or black) may appear in saliva, urine, or sweat after taking Stalevo. Although the color appears to be clinically insignificant, garments may become discolored.

Advise patients that a change in diet to foods that are high in protein may delay the absorption of levodopa. Excessive acidity also delays stomach emptying, thus delaying the absorption of levodopa. Iron salts (such as in multi-vitamin tablets) may also reduce the effectiveness of Stalevo.

Pregnancy

Instruct patients to notify their healthcare provider if they become pregnant or intend to become pregnant during therapy [see Use in Specific Populations (8.1)].

Lactation

Instruct patients to notify their healthcare provider if they intend to breastfeed or are breastfeeding an infant [see Use in Specific Populations (8.2)].

Manufactured by:

Orion Corporation
Orion Pharma, Orionintie 1
FI-02200 Espoo, Finland

Distributed by:

Almatica Pharma LLC

Morristown, NJ 07960 USA

Rev. 05/2020

PI805-00

PRINCIPAL DISPLAY PANEL - 100 Tablet Bottle Label - 805

NDC 52427-805-01

Stalevo® 50

carbidopa USP 12.5 mg
levodopa USP 50 mg
and
entacapone 200 mg

Rx only

100 Tablets

Do not combine tablets to achieve a higher strength
tablet due to the risk of entacapone overdose.

PRINCIPAL DISPLAY PANEL - 100 Tablet Bottle Label - 809

NDC 52427-809-01

Stalevo® 75

carbidopa USP 18.75 mg
levodopa USP 75 mg
and
entacapone 200 mg

Rx only

100 Tablets

Do not combine tablets to achieve a higher strength
tablet due to the risk of entacapone overdose.

PRINCIPAL DISPLAY PANEL - 100 Tablet Bottle Label - 816

NDC 52427-816-01

Stalevo® 100

carbidopa USP 25 mg
levodopa USP 100 mg
and
entacapone 200 mg

Rx only

100 Tablets

Do not combine tablets to achieve a higher strength
tablet due to the risk of entacapone overdose.

PRINCIPAL DISPLAY PANEL - 100 Tablet Bottle Label - 827

NDC 52427-827-01

Stalevo® 125

carbidopa USP 31.25 mg
levodopa USP 125 mg
and
entacapone 200 mg

Rx only

100 Tablets

Do not combine tablets to achieve a higher strength
tablet due to the risk of entacapone overdose.

PRINCIPAL DISPLAY PANEL - 100 Tablet Bottle Label - 834

NDC 52427-834-01

Stalevo® 150

carbidopa USP 37.5 mg
levodopa USP 150 mg
and
entacapone 200 mg

Rx only

100 Tablets

Do not combine tablets to achieve a higher strength
tablet due to the risk of entacapone overdose.

PRINCIPAL DISPLAY PANEL - 100 Tablet Bottle Label - 842

NDC 52427-842-01

Stalevo® 200

carbidopa USP 50 mg
levodopa USP 200 mg
and
entacapone 200 mg

Rx only

100 Tablets

Do not combine tablets to achieve a higher strength
tablet due to the risk of entacapone overdose.